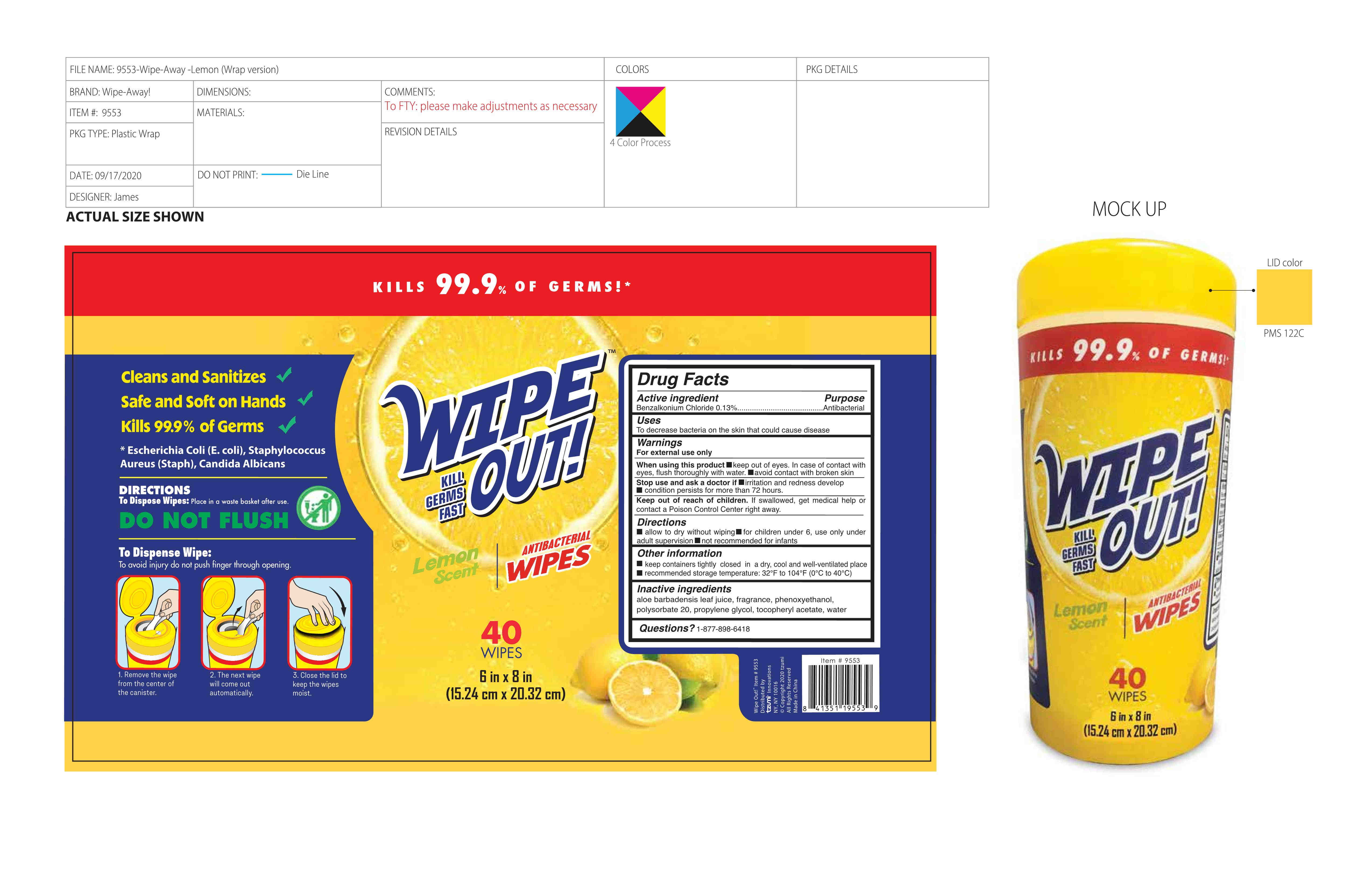 DRUG LABEL: Antibacterial Wipes
NDC: 92185-001 | Form: CLOTH
Manufacturer: Hangzhou Suncilia Yuehui Biotechnology Co., LTD
Category: otc | Type: HUMAN OTC DRUG LABEL
Date: 20201116

ACTIVE INGREDIENTS: BENZALKONIUM CHLORIDE 0.13 g/100 g
INACTIVE INGREDIENTS: WATER; ALOE VERA LEAF; .ALPHA.-TOCOPHEROL ACETATE; PHENOXYETHANOL; POLYSORBATE 20; PROPYLENE GLYCOL

Uses

To decrease bacteria on the skin that could cause disease

1.Remove the wipe from the center of the canister.
2.The next wipe will come out automatically.
3.Close the lid to keep the wipes moist.

Directions

allow to dry without wiping for children under 6, use only underadult supervision not recommended for infants

WARNINGS

For external use only

When using this product keep out of eyes. In case of contact with eyes, flush thoroughly with water.avoid contact with broken skin

Stop use and ask a doctor if irritation and redness developcondition persists for more than 72 hours.

Keep out of reach of children. lf swallowed, get medical help orcontact a Poison Control Center right away.

Other information

keep containers tightly closed in a dry, cool and well-ventilated place

recommended storage temperature: 32°F to 104°F(0°C to 40°c)

INACTIVE INGREDIENT

aloe barbadensis leaf juice, fragrance, phenoxyethanol,polysorbate 20, propylene glycol, tocopheryl acetate, water

ACTIVE INGREDIENT

Benzalkonium Chloride 0.13%

PURPOSE

Disinfection
Sterilization
No Rinseing